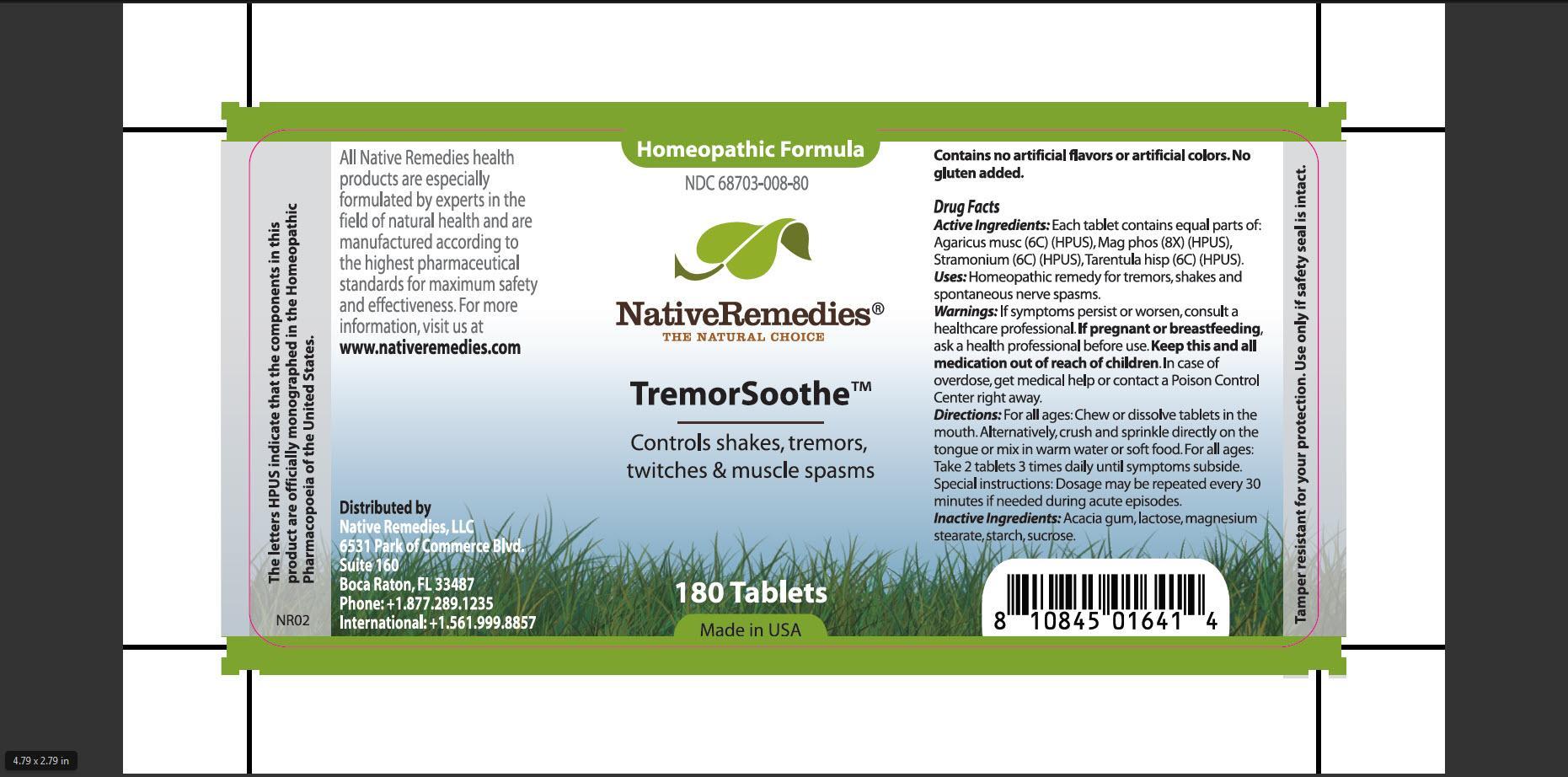 DRUG LABEL: TremorSoothe
NDC: 68703-008 | Form: TABLET
Manufacturer: Silver Star Brands, Inc
Category: homeopathic | Type: HUMAN OTC DRUG LABEL
Date: 20150716

ACTIVE INGREDIENTS: AMANITA MUSCARIA VAR. MUSCARIA FRUITING BODY 6 [hp_C]/1 1; MAGNESIUM PHOSPHATE, DIBASIC TRIHYDRATE 8 [hp_X]/1 1; DATURA STRAMONIUM 6 [hp_C]/1 1; LYCOSA TARANTULA 6 [hp_C]/1 1
INACTIVE INGREDIENTS: ACACIA; LACTOSE; MAGNESIUM STEARATE; STARCH, CORN; SUCROSE

TremorSoothe

PURPOSE

Controls shakes, tremors, twitches and muscle spasms

ACTIVE INGREDIENT

Active Ingredients: Each tablet contains equal parts of: Agaricus musc(6C) (HPUS), Mag phos (8X) (HPUS), Stramonium (6C) (HPUS), Tarentula hisp (6C) (HPUS)

INDICATIONS AND USAGE

Uses: Homeopathic remedy for tremors, shakes and spontaneous nerve spasms.

WARNINGS

Warnings:If symptoms persist or worsen, consult a healthcare professional.

PREGNANCY OR BREAST FEEDING

If pregnant of breastfeeding, ask health professional before use.

KEEP OUT OF REACH OF CHILDREN

Keep this and all medication out of reach of children

OVERDOSAGE

In case of overdose, get medical help or contact a Poison Control Center right away

DOSAGE AND ADMINISTRATION

Directions: For all ages: Chew or dissolve tablets in the mouth. Alternatively, crush and sprinkle directly on the tongue or mix in warm water or soft food. For all ages: Take 2 tablets 3 times daily until symptoms subside. Special instruction: Dosage may be repeat every 30 minutes if needed during acute episodes.

INACTIVE INGREDIENT

Inactive Ingredients: Acacia gum, lactose, magnesium stearate, starch, sucrose

PATIENT COUNSELING INFORMATION

The letters HPUS indicate that the components in this product are officially monographed in the Homeopathic Pharmacopoeia of the United States.

All Native Remedies health products are especially formulated by experts in the field of natural health and are manufactured according to the highest pharmaceutical standards for maximum safety and effectiveness. For more information, visit us at www.nativeremedies.com

Distributed by
Native Remedies, LLC
6531 Park of Commerce Blvd.
Suite 160
Boca Raton, Fl 33487
Phone:+1.877.289.1235
International:+1.561.999.8857

Contains no artificial flavors or artificial colors. No gluten added.

STORAGE AND HANDLING

Tamper resistant for your protection. Use only if safety seal is intact